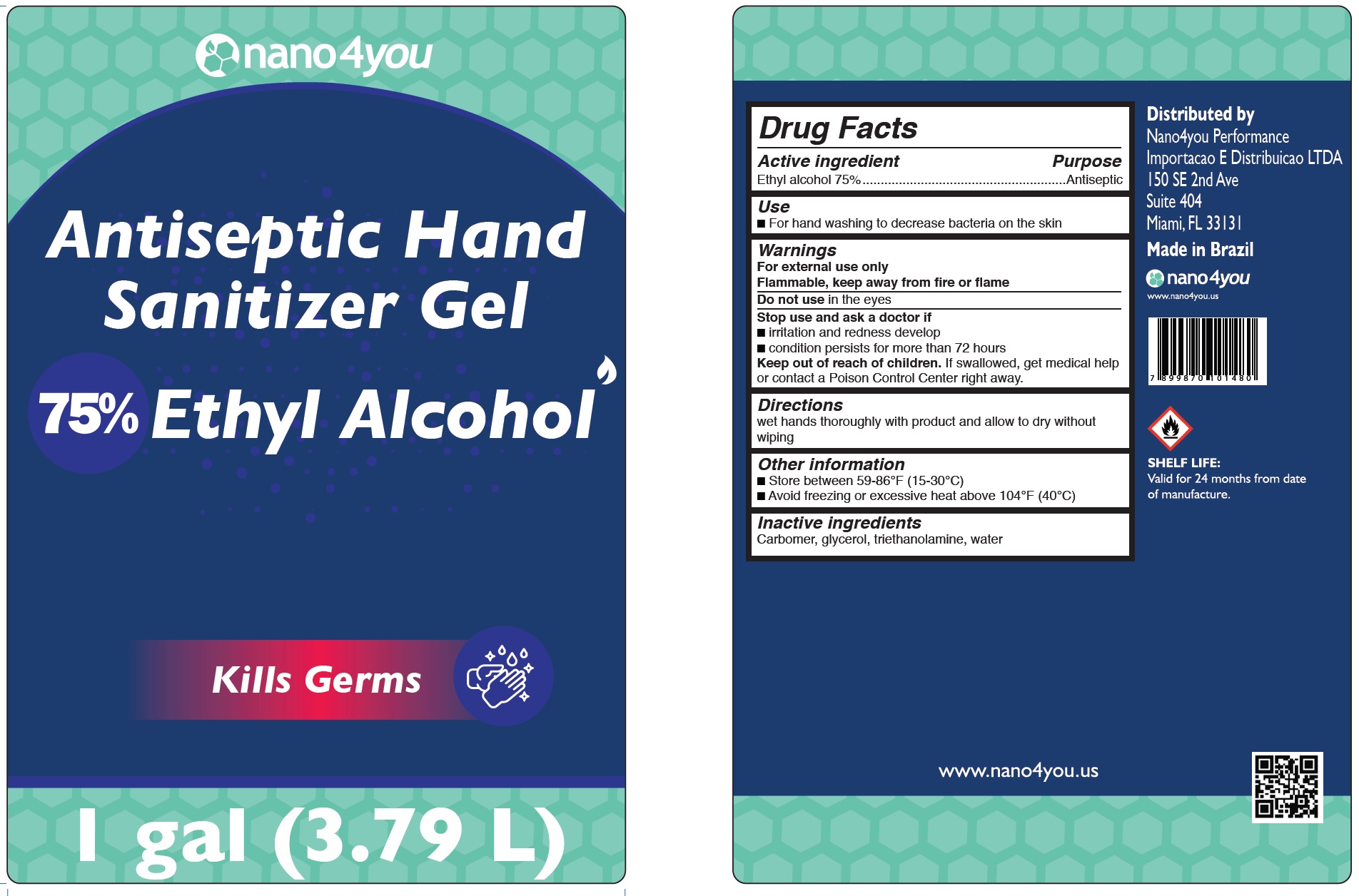 DRUG LABEL: Antiseptic Hand Sanitizer Gel, 75% Ethyl Alcohol
NDC: 79816-000 | Form: GEL
Manufacturer: Nano4you Performance Importacao E Distribuicao LTDA
Category: otc | Type: HUMAN OTC DRUG LABEL
Date: 20200831

ACTIVE INGREDIENTS: ALCOHOL 0.75 mL/1 mL
INACTIVE INGREDIENTS: CARBOMER HOMOPOLYMER, UNSPECIFIED TYPE; GLYCERIN; TROLAMINE; WATER

Antiseptic Hand Sanitizer Gel, 75% Ethyl Alcohol

Active ingredient

Ethyl alcohol 75%

Purpose

Antiseptic

Use

- For hand washing to decrease bacteria on the skin

Warnings

For external use only
Flammable, keep away from fire or flame

Do not use

in the eyes

Stop use and ask a doctor if

- irritation and redness develop
- condition persists for more than 72 hours

Keep out of reach of children.

If swallowed, get medical help or contact a Poison Control Center right away.

Directions

wet hands thoroughly with product and allow to dry without wiping

Other information

- Store between 59-86°F (15-30°C)
- Avoid freezing or excessive heat above 104°F (40°C)

Inactive ingredients

Carbomer, glycerol, triethanolamine, water